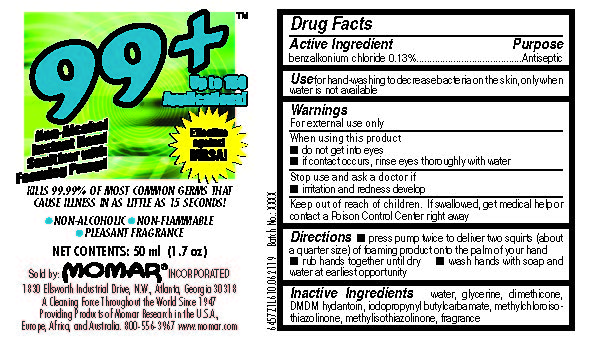 DRUG LABEL: 99 Plus Hand Sanitizer
NDC: 63533-457 | Form: LIQUID
Manufacturer: Momar Incorporated
Category: otc | Type: HUMAN OTC DRUG LABEL
Date: 20260106

ACTIVE INGREDIENTS: BENZALKONIUM CHLORIDE 1.3 mg/1 mL
INACTIVE INGREDIENTS: WATER; GLYCERIN; DIMETHICONE; DMDM HYDANTOIN; IODOPROPYNYL BUTYLCARBAMATE; METHYLCHLOROISOTHIAZOLINONE; METHYLISOTHIAZOLINONE

99 Plus Instant Hand Sanitizer Drug Facts and Label

Drug Facts Box OTC-Active Ingredient Section

benzalkonium chloride USP 0.13%

Drug Facts Box OTC-Indications & Usage Section

For hand-washing to decrease bacteria on the skin, only when water is not available

Drug Facts Box OTC-Warnings Section

For external use only

Drug Facts Box OTC-Purpose Section

Antiseptic

Drug Facts Box-OTC When Using Section

do not get into eyes

if contact occurs, rinse eyes thoroughly with water

Drug Facts Box-OTC Stop Use Section

irritation and redness develop

Drug Facts Box-OTC Keep Out Of Reach Of Children Section

If swallowed, get medical help or contact a Poison Control Center right away

Drug Facts Box-OTC Dosage & Administration Section

press pump twice to deliver two squirts (about a quarter size) of foaming product onto the palm of your hand

rub hands together until dry

wash hands with soap and water at earliest opportunity

Drug Facts Box-OTC Inactive Ingredient Section

water, glycerine, dimethicone, DMDM hydantoin, iodopropynl butylcarbamate, methylchloroisothiazolinone, methylisothiazolinone, fragrance

99 Plus Instant Hand Sanitizer